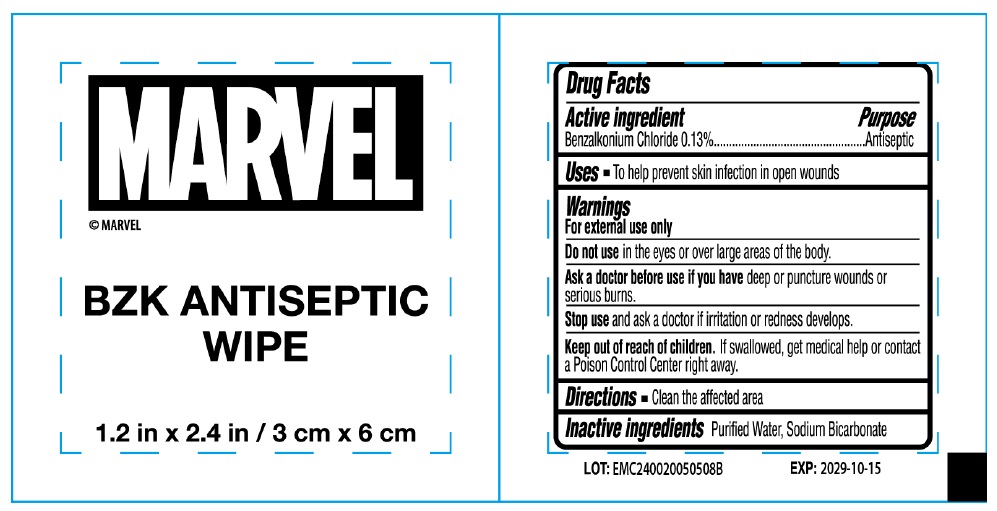 DRUG LABEL: MARVEL BZK ANTISEPTIC WIPE
NDC: 70108-104 | Form: CLOTH
Manufacturer: Ashtel Studios, Inc.
Category: otc | Type: HUMAN OTC DRUG LABEL
Date: 20241118

ACTIVE INGREDIENTS: BENZALKONIUM CHLORIDE 0.13 g/100 mL
INACTIVE INGREDIENTS: WATER; SODIUM BICARBONATE

MARVEL BZK ANTISEPTIC WIPE

Active ingredient

Benzalkonium Chloride 0.13%

Purpose

Antiseptic

Uses

• To help prevent skin infection in open wounds

Warnings

For external use only

Do not use in the eyes or over large areas of the body.

Ask a doctor before use if you have deep or puncture wounds or serious burns.

Stop use and ask a doctor if irritation or redness develops.

Keep out of reach of children. If swallowed, get medical help or contact a Poison Control Center right away.

Directions

• Clean the affected area

Inactive ingredients

Purified Water, Sodium Bicarbonate

© MARVEL